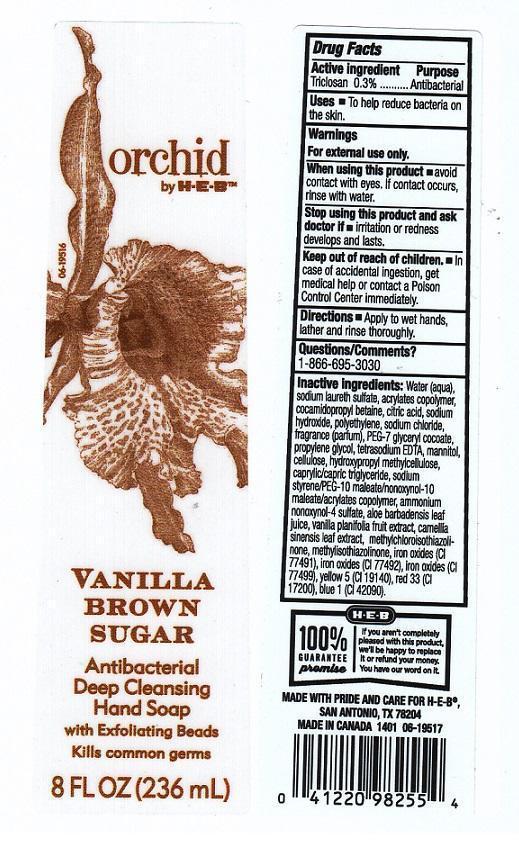 DRUG LABEL: ORCHID BY H E B
NDC: 37808-201 | Form: LIQUID
Manufacturer: H E B
Category: otc | Type: HUMAN OTC DRUG LABEL
Date: 20140304

ACTIVE INGREDIENTS: ALCOHOL 650 mg/1 mL
INACTIVE INGREDIENTS: WATER; SODIUM LAURETH SULFATE; METHACRYLIC ACID - METHYL METHACRYLATE COPOLYMER (1:1); COCAMIDOPROPYL BETAINE; CITRIC ACID MONOHYDRATE; SODIUM HYDROXIDE; HIGH DENSITY POLYETHYLENE; SODIUM CHLORIDE; PEG-7 GLYCERYL COCOATE; PROPYLENE GLYCOL; EDETATE SODIUM; MANNITOL; POWDERED CELLULOSE; HYPROMELLOSES; MEDIUM-CHAIN TRIGLYCERIDES; AMMONIUM NONOXYNOL-4 SULFATE; ALOE VERA LEAF; VANILLA; GREEN TEA LEAF; METHYLCHLOROISOTHIAZOLINONE; METHYLISOTHIAZOLINONE; FERRIC OXIDE RED; FERRIC OXIDE YELLOW; FERROSOFERRIC OXIDE; FD&C YELLOW NO. 5; D&C RED NO. 33; FD&C BLUE NO. 1

DRUG FACTS

ACTIVE INGREDIENT

ETHYL ALCOHOL 65%

PURPOSE

ANTIBACTERIAL

USES

TO HELP REDUCE BACTERIA ON THE SKIN

WARNINGS

FOR EXTERNAL USE ONLY

WHEN USING THIS PRODUCT

AVOID CONTACT WITH EYES. IF CONTACT OCCURS, RINSE WITH WATER

STOP USING THIS PRODUCT AND ASK DOCTOR IF

IRRITATION OR REDNESS DEVELOPS AND LASTS

KEEP OUT OF REACH OF CHILDREN

IN CASE OF ACCIDENTAL INGESTION, GET MEDICAL HELP OR CONTACT A POISON CONTROL CENTER IMMEDIATELY

DIRECTIONS

APPLY TO WET HANDS, LATHER AND RINSE THOROUGHLY

QUESTIONS/COMMENTS?

1-866-695-3030

INACTIVE INGREDIENTS

WATER (AQUA), SODIUM LAURETH SULFATE, ACRYLATES COPOLYER, COCAMIDOPROPYL BETAINE, CITRIC ACID, SODIU HYDROXIDE, POLYETHYLENE, SODIUM CHLORIDE, FRAGRANCE (PARFUM), PEG-7 GLYCERYL COCOATE, PROPYLENE GLYCOL, TETRASODIUM EDTA, MANNITOL, CELLULOSE, HYDROXYPROPYL METHYLCELLULOSE, CAPRYLIC/CAPRIC TRIGLYCERIDE, SODIUM STYRENE/PEG-10 MALEATE/NONOXYNOL-10 MALEATE/ACRYLATES COPOLYMER, AMMONIUM NONOXYNOL-4 SULFATE, ALOE BARBADENSIS LEAF JUICE, VANILLA PLANIFOLIA FRUIT EXTRACT, CAMELLIA SINENSIS LEAF EXTRACT, METHYLCHLOROISOTHIAZOLINONE, METHYLISOTHIAZOLINONE, IRON OXIDES (CI 77491), IRON OXIDES (CI 77492), IRON OXIDES (CI 77499), YELLOW 5 (CI 19140), RED 33 (CI 17200), BLUE 1 (CI 42090)